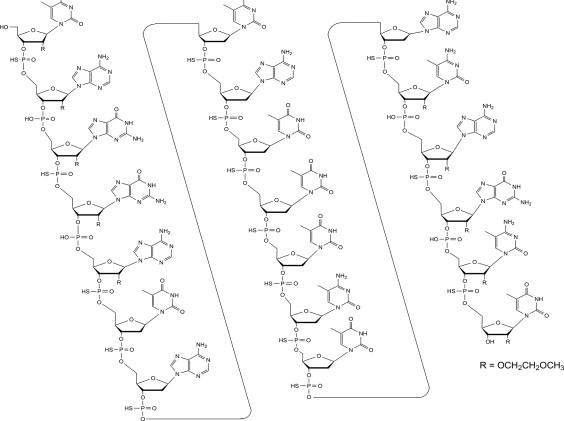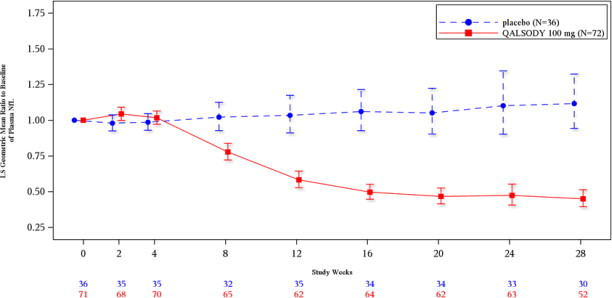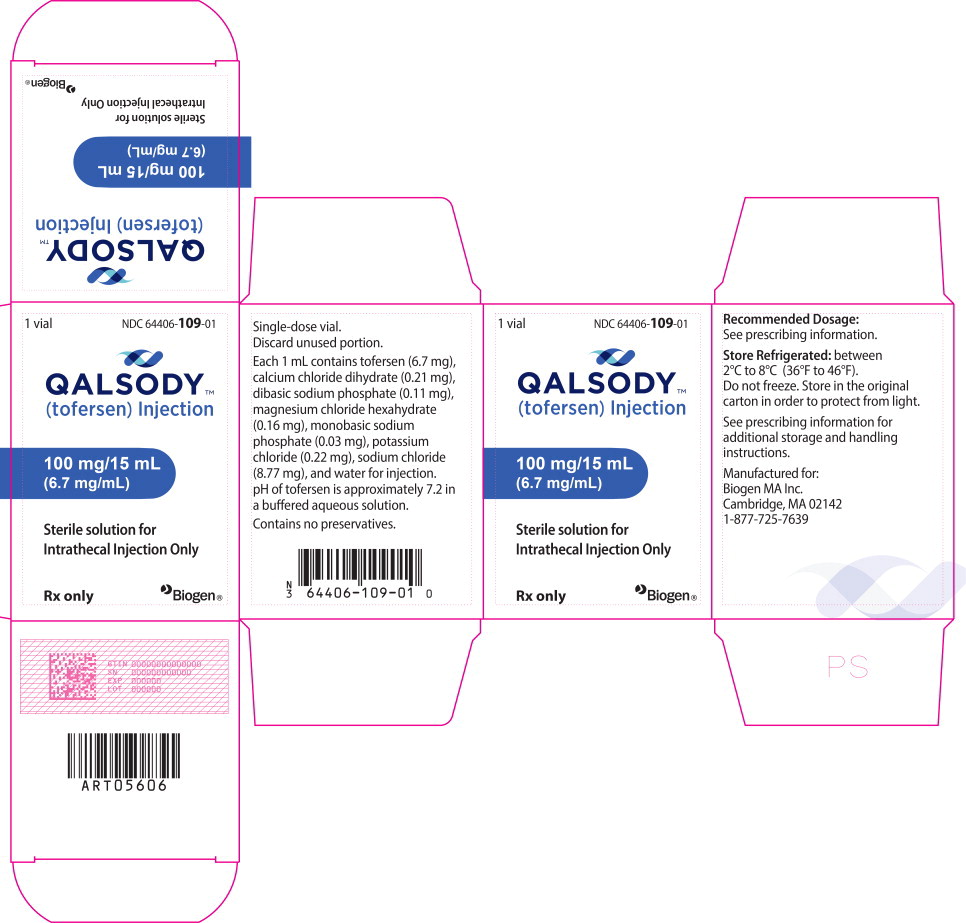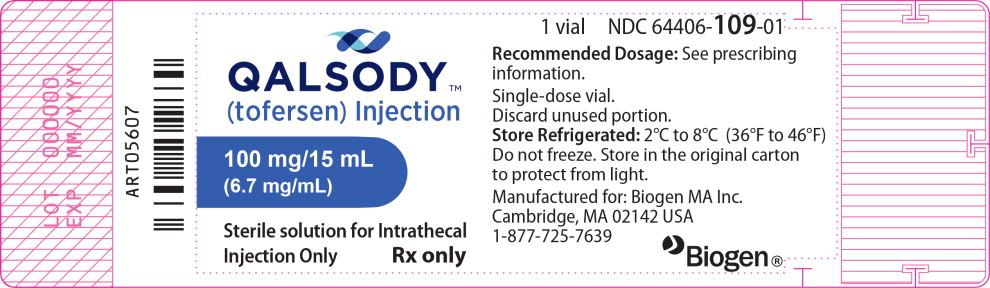 DRUG LABEL: QALSODY
NDC: 64406-109 | Form: INJECTION
Manufacturer: Biogen Inc.
Category: prescription | Type: HUMAN PRESCRIPTION DRUG LABEL
Date: 20241113

ACTIVE INGREDIENTS: tofersen 100 mg/15 mL
INACTIVE INGREDIENTS: sodium phosphate, monobasic, unspecified form; sodium phosphate, dibasic, unspecified form; sodium chloride; potassium chloride; calcium chloride; magnesium chloride; water

HIGHLIGHTS OF PRESCRIBING INFORMATION

These highlights do not include all the information needed to use QALSODY ™ safely and effectively. See full prescribing information for QALSODY.
QALSODY (tofersen) injection, for intrathecal use
Initial U.S. Approval: 2023

1 INDICATIONS AND USAGE

QALSODY is an antisense oligonucleotide indicated for the treatment of amyotrophic lateral sclerosis (ALS) in adults who have a mutation in the superoxide dismutase 1 (SOD1) gene. This indication is approved under accelerated approval based on reduction in plasma neurofilament light chain observed in patients treated with QALSODY. Continued approval for this indication may be contingent upon verification of clinical benefit in confirmatory trial(s). (1)

2 DOSAGE AND ADMINISTRATION

QALSODY is administered intrathecally (2.1)

Dosing Information (2.1)

- Recommended dose: 100 milligrams (15 mL) per administration
- Initiate QALSODY treatment with 3 loading doses administered at 14day intervals. A maintenance dose should be administered once every 28 days thereafter.

Preparation and Administration Instructions (2.2)

- Allow to warm to room temperature prior to administration
- Administer within 4 hours of removal from vial
- Prior to administration, remove approximately 10 mL of cerebrospinal fluid
- Administer as an intrathecal bolus injection over 1 to 3 minutes

3 DOSAGE FORMS AND STRENGTHS

Injection: 100 mg/15 mL (6.7 mg/mL) solution in a single-dose vial (3)

4 CONTRAINDICATIONS

None (4)

5 WARNINGS AND PRECAUTIONS

- Myelitis and/ or Radiculitis: Serious events of myelitis and radiculitis have been reported. Monitor for symptoms; diagnostic workup and treatment should be initiated according to the standard of care. (5.1)
- Papilledema and Elevated Intracranial Pressure: Serious events of papilledema and elevated intracranial pressure have been reported. Monitor for symptoms; diagnostic workup and treatment should be initiated according to standard of care. (5.2)
- Aseptic Meningitis: Serious events of aseptic meningitis have been reported. Monitor for symptoms; diagnostic workup and treatment should be initiated according to standard of care. (5.3)

6 ADVERSE REACTIONS

The most common adverse reactions (≥ 10% of patients treated with QALSODY and greater than placebo) were pain, fatigue, arthralgia, cerebrospinal fluid white blood cell increased, and myalgia. (Section 6.1)

To report SUSPECTED ADVERSE REACTIONS, contact Biogen at 1-877-725-7639 or FDA at 1-800-FDA-1088 or www.fda.gov/medwatch.

FULL PRESCRIBING INFORMATION

1 INDICATIONS AND USAGE

QALSODY is indicated for the treatment of amyotrophic lateral sclerosis (ALS) in adults who have a mutation in the superoxide dismutase 1 (SOD1) gene. This indication is approved under accelerated approval based on reduction in plasma neurofilament light chain (NfL) observed in patients treated with QALSODY [see Clinical Studies (14)]. Continued approval for this indication may be contingent upon verification of clinical benefit in confirmatory trial(s).

2 DOSAGE AND ADMINISTRATION

2.1. Dosing Information

Recommended Dosage

Administer QALSODY intrathecally using a lumbar puncture by, or under the direction of, healthcare professionals experienced in performing lumbar punctures.

The recommended dosage is 100 mg (15 mL) of QALSODY per administration.

Initiate QALSODY treatment with three (3) loading doses administered at 14-day intervals.

Administer a maintenance dose every 28 days thereafter.

Missed Dose

If the second loading dose is missed, administer QALSODY as soon as possible, and administer the third loading dose 14 days later.

If the third loading dose or a maintenance dose is missed, administer QALSODY as soon as possible, and administer the next dose 28 days later.

2.2. Preparation and Administration Instructions

Use aseptic technique when preparing and administering QALSODY intrathecally. Prepare and administer QALSODY according to the following steps:

Preparation

Vial preparation instructions

- Allow refrigerated QALSODY vial to warm to room temperature (25°C/77°F) prior to administration without using external heat sources [see Storage and Handling (16.2)].
- Inspect the solution in the QALSODY vial prior to administration. Do not administer if particles are observed or the liquid in the vial is not clear and colorless to slightly yellow.
- Do not shake the QALSODY vial.

Procedural preparation instructions

- If indicated by the clinical condition of the patient, consider sedation.
- If indicated by the clinical condition of the patient, consider imaging to guide intrathecal administration of QALSODY.
- Prior to removing the vial's cap on the aluminum overseal, confirm readiness of the patient. An unopened QALSODY vial can be returned to the refrigerator [see Storage and Handling (16.2)].
- Evaluate patients prior to and after intrathecal injection for the presence of potential conditions related to lumbar puncture, to avoid serious procedural complications.

Administration

Prior to administration, remove approximately 10 mL of cerebrospinal spinal fluid (CSF) using a lumbar puncture needle.

Prior to administration, remove the plastic cap and attach a needle to the syringe, for the purpose of withdrawing QALSODY from the vial. Insert the needle into the vial through the center of the overseal and withdraw the required dose of 15 mL (equivalent to 100 mg) from the vial.

- Do not dilute QALSODY.
- External filters are not required.

Administer QALSODY using a lumbar puncture needle as an intrathecal bolus injection over 1 to 3 minutes.

- QALSODY contains no preservatives. Once drawn into the syringe, the solution should be administered immediately (within 4 hours of removal from the vial) at room temperature; otherwise, it must be discarded.

Any unused contents of the single-dose vial should be discarded.

3 DOSAGE FORMS AND STRENGTHS

Injection: 100 mg/15 mL (6.7 mg/mL) as a clear and colorless to slightly yellow solution in a single-dose vial.

4 CONTRAINDICATIONS

None.

5 WARNINGS AND PRECAUTIONS

5.1. Myelitis and/or Radiculitis

Serious adverse reactions of myelitis and radiculitis have been reported in patients treated with QALSODY. Six patients treated with QALSODY experienced myelitis or radiculitis in the clinical studies. Two patients discontinued treatment with QALSODY and required symptomatic management with full resolution of symptoms. In the remaining 4 patients, symptoms resolved without discontinuation of QALSODY. If symptoms consistent with myelitis or radiculitis develop, diagnostic workup and treatment should be initiated according to the standard of care. Management may require interruption or discontinuation of QALSODY.

5.2. Papilledema and Elevated Intracranial Pressure

Serious adverse reactions of papilledema and elevated intracranial pressure have been reported in patients treated with QALSODY. Four patients developed elevated intracranial pressure and/or papilledema. All patients received treatment with standard of care with resolution of symptoms, and no events led to discontinuation of QALSODY. If symptoms consistent with papilledema or elevated intracranial pressure develop, diagnostic workup and treatment should be initiated according to the standard of care.

5.3. Aseptic Meningitis

Serious adverse reactions of aseptic meningitis (also called chemical meningitis or drug-induced aseptic meningitis) have been reported in patients treated with QALSODY. One patient experienced a serious adverse reaction of chemical meningitis, which led to discontinuation of QALSODY. One patient experienced a serious adverse reaction of aseptic meningitis, which did not lead to discontinuation of QALSODY. In addition, nonserious adverse drug reactions of CSF white blood cell increased, and CSF protein increased have also been reported with QALSODY [see Adverse Reactions (6.1)]. If symptoms consistent with aseptic meningitis develop, diagnostic workup and treatment should be initiated according to the standard of care.

6 ADVERSE REACTIONS

The following clinically significant adverse reactions are discussed elsewhere in the labeling:

- Myelitis and/or Radiculitis [see Warnings and Precautions (5.1)]
- Papilledema and Elevated Intracranial Pressure [see Warnings and Precautions (5.2)]
- Aseptic Meningitis [see Warnings and Precautions (5.3)]

6.1. Clinical Trials Experience

Because clinical trials are conducted under widely varying conditions, adverse reaction rates observed in the clinical trials of QALSODY cannot be directly compared to rates in clinical trials of other drugs and may not reflect the rates observed in practice.

The safety of QALSODY 100 mg was evaluated in 147 patients with SOD1-ALS. The median patient exposure was 119.4 weeks (range from 4 to 212 weeks). QALSODY was evaluated in the placebo-controlled Study 1 and in the open label extension Study 2. In Study 1 Part C, approximately 43% were female; 57% were male; 64% were White and 8% were Asian. The mean age at entry in Study 1 Part C was 49.8 years (range from 23 to 78 years).

The most common adverse reactions (≥ 10% of patients treated with QALSODY and greater than placebo) were pain, fatigue, arthralgia, CSF white blood cell increased, and myalgia. Table 1 shows the common adverse reactions that occurred in at least 5% of patients treated with QALSODY and at a 5% or higher frequency than placebo.

Table 1: Adverse Drug Reactions That Occurred in At Least 5% of Patients Treated with QALSODY and at >5% Higher Frequency Than Placebo
Adverse Reaction | Study 1 Part C
Adverse Reaction | QALSODY 100 mg (n = 72) % | Placebo (n = 36) %
Pain‡‡ | 42 | 22
Fatigue | 17 | 6
Arthralgia | 14 | 6
CSF white blood cell increased* | 14 | 0
Myalgia | 14 | 6
CSF protein increased | 8 | 3
Musculoskeletal stiffness | 6 | 0
Neuralgia | 6 | 0
‡‡ Pain includes preferred terms of pain, back pain, and pain in extremity.
* CSF white blood cell increased includes preferred terms of CSF white blood cell increased and pleocytosis.

Less Common Adverse Reactions

Serious adverse reactions of myelitis and radiculitis; papilledema and elevated intracranial pressure; and aseptic meningitis have occurred in patients treated with QALSODY [see Warnings and Precautions (5.1, 5.2, 5.3)].

In the long-term extension study, nonserious adverse reactions of pyrexia have occurred with repeat administration of QALSODY.

8 USE IN SPECIFIC POPULATIONS

8.1. Pregnancy

Risk Summary

There are no adequate data on developmental risks associated with the use of QALSODY in pregnant women to evaluate for a drug-associated risk of major birth defects, miscarriage, or other adverse maternal or fetal outcomes. In the U.S. general population, the estimated background risk of major birth defects and miscarriage in clinically recognized pregnancies is 2 to 4% and 15 to 20%, respectively. The background risk of major birth defects and miscarriage for the indicated population is unknown.

Data

Animal Data

Subcutaneous administration of tofersen (0, 3, 10, 30 mg/kg) every other day to pregnant mice during the period of organogenesis resulted in no adverse effects on embryofetal development. Plasma exposure at the highest dose tested (30 mg/kg) was approximately 4 times that in humans at the recommended human dose (RHD) of 100 mg.

Subcutaneous administration of tofersen (0, 3, 10, 30 mg/kg) every other day to pregnant rabbits during the period of organogenesis resulted in no adverse effects on embryofetal development. Plasma exposure at the highest dose tested (30 mg/kg) was approximately 20 times that in humans at the RHD.

Subcutaneous administration of tofersen (0, 3, 10, or 30 mg/kg) every other day to male and female mice prior to and during mating and continuing in females throughout organogenesis resulted in no adverse effects on pre- or postnatal development. Plasma exposures at the highest dose tested (30 mg/kg) were approximately 4 times that in humans at the RHD.

8.2. Lactation

Risk Summary

There are no data on the presence of tofersen or its metabolites in human milk, the effects on the breastfed infant, or the effects on milk production. Tofersen was detected in the milk of lactating mice following subcutaneous administration. The developmental and health benefits of breastfeeding should be considered along with the mother's clinical need for QALSODY and any potential adverse effects on the breastfed infant from QALSODY or from the underlying maternal condition.

8.4. Pediatric Use

Safety and effectiveness in pediatric patients have not been established.

8.5. Geriatric Use

A total of 13.5% (22/162) patients were 65 years of age and older and 1.2% (2/162) patients were 75 years of age and older at initiation of treatment in clinical studies for ALS in patients who have a mutation in the superoxide dismutase 1 (SOD1) gene [see Clinical Studies (14)]. No overall differences in safety or effectiveness were observed between these patients and younger patients, but a greater sensitivity of some older individuals cannot be ruled out. There is no evidence for special dosage considerations based on age when QALSODY is administered.

11 DESCRIPTION

Tofersen, an antisense oligonucleotide, is a 20-base residue (20-mer) 5-10-5 MOE gapmer mixed backbone oligonucleotide. Of the nineteen internucleotide linkages, fifteen are 3′-O to 5′-O phosphorothioate diesters, and four are 3′-O to 5′-O phosphate diesters. Ten of the twenty sugar residues are 2-deoxy-D-ribose and the remainder are 2′-O-(2-methoxyethyl)-D-ribose (MOE). The residues are arranged so that there are five MOE nucleosides at the 5′ and 3′-ends of the molecule flanking a gap of ten 2′-deoxynucleosides. The cytosine and uridine bases are methylated at the 5-position. The structural formula is:

Figure 1: Structural Formula for Tofersen

The molecular formula is C230 H317 N72 O123 P19 S15 and the molecular weight is 7127.86 atomic mass units (amu).

QALSODY is supplied as a sterile, preservative-free, clear, and colorless to slightly yellow solution in a Type I glass vial to be administered by intrathecal administration. Each vial of drug product contains a single dose of 100 mg tofersen at a concentration of 6.7 mg/mL in a formulation containing 0.21 mg/mL calcium chloride dihydrate, 0.11 mg/mL dibasic sodium phosphate, 0.16 mg/mL magnesium chloride hexahydrate, 0.03 mg/mL monobasic sodium phosphate, 0.22 mg/mL potassium chloride, 8.77 mg/mL sodium chloride, and water for injection. The pH of QALSODY is approximately 7.2 (range 6.7 to 7.7).

12 CLINICAL PHARMACOLOGY

12.1. Mechanism of Action

Tofersen is an antisense oligonucleotide that causes degradation of SOD1 mRNA through binding to SOD1 mRNA, which results in a reduction of SOD1 protein synthesis.

12.2. Pharmacodynamics

Effect of Tofersen on Total CSF SOD1 Protein

Total CSF SOD1, an indirect measure of target engagement, was evaluated in Study 1 Part C in SOD1-ALS patients [see Clinical Studies (14)].

At Week 28 in Study 1 Part C, a reduction in total CSF SOD1 protein of 35% (geometric mean ratio to baseline) in the tofersen-treated group versus a 2% decrease from baseline in the corresponding placebo subjects in the ITT population was observed (difference in geometric mean ratios for tofersen to placebo: 34%; nominal p<0.0001).

Effect of Tofersen on Neurofilament Proteins

Plasma NfL, a blood-based biomarker of axonal injury and neurodegeneration, was evaluated in Study 1 Part C in SOD1-ALS patients [see Clinical Studies (14)].

At Week 28 in Study 1 Part C, mean plasma NfL was reduced 55% (geometric mean ratio to baseline) in the QALSODY-treated subjects, compared to a 12% increase with placebo in ITT population (difference in geometric mean ratios for QALSODY to placebo: 60%; nominal p<0.0001). Plasma NfL declined until approximately Day 113, after which the reductions were sustained. The reductions in phosphorylated neurofilament heavy chain (pNfH) were similar compared to reductions in NfL, as were reductions in CSF compared to plasma.

Cardiac Electrophysiology

At the maximum approved recommended dosing regimen, QALSODY does not prolong the QTc interval to any clinically relevant extent.

12.3. Pharmacokinetics

Absorption

Intrathecal administration of QALSODY into the CSF allows tofersen to be distributed from the CSF to central nervous system tissues. The maximum CSF trough concentration occurred at the third dose, which was the last dose of the loading period. There was little to no accumulation for CSF tofersen with monthly dosing after the loading phase. Tofersen is transferred from CSF into the systemic circulation, with median time to maximum concentration (Tmax) plasma values ranging from 2 to 6 hours. There was no accumulation in plasma tofersen exposure following monthly maintenance dosing.

Distribution

Autopsy tissue from patients treated with tofersen (n=3) showed that tofersen administered intrathecally was distributed within the central nervous system tissues.

Elimination

Metabolism

Tofersen is expected to be metabolized through exonuclease (3'- and 5')-mediated hydrolysis and is not a substrate for, or inhibitor or inducer of CYP450 enzymes.

Excretion

The primary route of elimination has not been characterized. The effective half-life in CSF is estimated to be 4 weeks.

Drug Interaction Studies

No clinical drug interaction studies have been performed. In vitro, QALSODY is not a substrate or inhibitor/inducer of major CYP enzymes or a substrate or inhibitor of major transporters.

Specific Populations

Effect of sex, race, age, and body weight on tofersen exposure in plasma was not clinically significant. The effect of these factors on tofersen exposure in CSF is unknown.

Patients with Renal or Hepatic Impairment

No clinical studies have been conducted to evaluate the pharmacokinetics of tofersen in patients with renal or hepatic impairment. Tofersen is not expected to undergo metabolism by hepatic enzymes.

12.6. Immunogenicity

As with all therapeutic oligonucleotides, there is a potential for immunogenicity.

Immunogenicity assay results are highly dependent on the sensitivity and specificity of the assay and may be influenced by several factors such as: assay methodology, sample handling, timing of sample collection, concomitant medications, and underlying disease. For these reasons, comparison of the incidence of antibodies to tofersen with the incidence of antibodies to other products may be misleading.

The immunogenic response to QALSODY was evaluated in 166 patients with post-baseline plasma samples for anti-drug antibodies (ADAs). Overall, 97 QALSODY-treated patients (58.4%) developed treatment-emergent ADAs, of which 14 were transient and 83 were persistent. The presence of anti-drug antibodies (ADA) appeared to decrease plasma tofersen clearance by 32%. Effects of ADA on CSF tofersen clearance is unknown. No discernible effects of ADAs on total SOD1 protein reduction or plasma NfL reduction have been observed. No discernible effects of ADAs on safety (incidence of AEs including hypersensitivity, anaphylactic reaction, and angioedema) have been observed. Medical review of individual cases of serious neurological events also showed no association with ADA status.

13 NONCLINICAL TOXICOLOGY

13.1. Carcinogenesis, Mutagenesis, Impairment of Fertility

Carcinogenesis

Studies to assess the carcinogenic potential of tofersen have not been conducted.

Mutagenesis

Tofersen was negative in in vitro (bacterial reverse mutation and mammalian cell chromosomal aberration) and in vivo (mouse micronucleus) assays.

Impairment of Fertility

In a study to assess effects on fertility and reproductive function, tofersen (0, 3, 10, 30 mg/kg) was administered every other day to male and female mice prior to and during mating and continuing in females to gestation day (GD) 7. Adverse effects on male reproductive organs (seminiferous tubular degeneration, seminiferous tubule dilatation, spermatid retention, apoptosis of epithelial cells, increased cellular debris in the testes, and hypospermia in the epididymis) were observed at the highest dose tested; however, there were no adverse effects on functional endpoints. Plasma exposure at the no-effect dose (10 mg/kg) for adverse effects on male reproductive organs was approximately 2 times that in humans at the recommended human dose of 100 mg.

14 CLINICAL STUDIES

The efficacy of QALSODY was assessed in a 28-week randomized, double-blind, placebocontrolled clinical study in patients 23 to 78 years of age with weakness attributable to ALS and a SOD1 mutation confirmed by a central laboratory (Study 1 Part C, NCT02623699). One hundred eight (108) patients were randomized 2:1 to receive treatment with either QALSODY 100 mg (n = 72) or placebo (n = 36) for 24 weeks (3 loading doses followed by 5 maintenance doses). Concomitant riluzole and/or edaravone use was permitted for patients.

The prespecified primary analysis population (n = 60, modified intent to treat [mITT]) had a slow vital capacity (SVC) ≥ 65% of predicted value and met prognostic enrichment criteria for rapid disease progression, defined based on their pre-randomization ALS Functional Rating Scale–Revised (ALSFRS-R) decline slope and SOD1 mutation type.

The non-mITT population (n = 48) had a slow vital capacity (SVC) ≥ 50% of predicted value and did not meet the enrichment criteria for rapid disease progression.

Baseline disease characteristics in the overall intent-to-treat (ITT) population (combined mITT and non-mITT population) were generally similar in patients treated with QALSODY and patients who received placebo, with slightly shorter time from symptom onset and higher plasma NfL at baseline in the QALSODY group. At baseline, 62% of patients were taking riluzole, and 8% of patients were taking edaravone. Mean baseline ALSFRS-R score was 36.9 (5.9) in the QALSODY treatment group and 37.3 (5.8) in the placebo group. Median time from symptom onset was 11.4 months in the QALSODY treatment group and 14.6 months in the placebo group.

The primary efficacy analysis was the change from baseline to Week 28 in the ALSFRS-R total score in the mITT population, analyzed using the joint rank test to account for mortality in conjunction with multiple imputation (MI) to account for missing data for withdrawals other than death. Patients treated with QALSODY experienced less decline from baseline in the ALSFRS-R compared to placebo, but the results were not statistically significant (QALSODY-placebo adjusted mean difference [95% CI]: 1.2 [-3.2, 5.5]). Other clinical secondary outcomes also did not reach statistical significance.

Secondary endpoints of change from baseline at Week 28 in plasma NfL and CSF SOD1 protein were nominally statistically significant (see Table 2). NfL reduction was consistently observed for all subgroups based on sex, disease duration since symptom onset, site of onset, and riluzole/edaravone use.

Table 2: Biomarker Results of QALSODY in Study 1 Part C at Week 28
Biomarker Endpoints | QALSODY | Placebo
Plasma NfL
ITT population | N=72 | N=36
Adjusted geometric mean ratio to baseline | 0.45 | 1.12
QALSODY to placebo difference in geometric mean ratio (95% CI) | 0.40 (0.33, 0.49)
Nominal p-value (ANCOVA+MI) | <0.0001
mITT population | N=39 | N=21
Adjusted geometric mean ratio to baseline | 0.40 | 1.20
QALSODY to placebo difference in geometric mean ratio (95% CI) | 0.33 (0.25, 0.45)
Nominal p-value (ANCOVA+MI) | <0.0001
CSF SOD1 Protein
ITT population | N=72 | N=36
Adjusted geometric mean ratio to baseline | 0.65 | 0.98
QALSODY to placebo difference in geometric mean ratio (95% CI) Nominal p-value (ANCOVA+MI) | 0.66 (0.57, 0.77) <0.0001
mITT population | N=39 | N=21
Adjusted geometric mean ratio to baseline | 0.71 | 1.16
QALSODY to placebo difference in geometric mean ratio (95% CI) | 0.62 (0.49, 0.78)
Nominal p-value (ANCOVA+MI) | <0.0001
Note 1: N is the number of patients with baseline value.
Note 2: MI was used for missing data. Model included treatment, use of riluzole or edaravone, relevant baseline score and postbaseline values (natural log transformed data). Separate models for mITT and nonmITT were used and combined for ITT analyses.
Note 3: Adjusted geometric mean ratios to baseline, treatment differences in adjusted geometric mean ratios to baseline and corresponding 95% CIs and nominal p-values were obtained from the ANCOVA model for change from baseline including treatment as a fixed effect and adjusting for the following covariates: baseline disease duration since symptom onset, relevant baseline score, and use of riluzole or edaravone. The analysis was based on natural log transformed data.

Figure 2: Plasma NfL Adjusted Geometric Mean Ratio to Baseline Values in Study 1 Part C by Study Week for the ITT Population

After completion of Study 1, patients had the option to enroll in an open-label extension study. At an interim analysis at 52 weeks, reductions in NfL were seen in patients previously receiving placebo who initiated QALSODY in the open-label extension study, similar to the reductions seen in patients treated with QALSODY in Study 1. Earlier initiation of QALSODY compared to placebo/delayed initiation of QALSODY was associated with trends for reduction in decline on ALSFRS-R, SVC percent-predicted, and hand-held dynamometry (HHD) megascore that were not statistically significant. Through all open-label follow-up at the time of the interim analysis, earlier initiation of QALSODY was also associated with a trend towards reduction of the risk of death or permanent ventilation, although it was not statistically significant. These exploratory analyses should be interpreted with caution given the limitations of data collected outside of a controlled study, which may be subject to confounding.

16 HOW SUPPLIED/STORAGE AND HANDLING

16.1. How Supplied

QALSODY injection is a sterile, clear and colorless to slightly yellow solution supplied as 100 mg/15 mL (6.7 mg/mL) solution in a single-dose glass vial free of preservatives.

The NDC is 64406-109-01.

16.2. Storage and Handling

Store refrigerated between 2°C to 8°C (36°F to 46°F) in the original carton to protect from light. Do not freeze.

If no refrigeration is available, QALSODY may be stored in its original carton, protected from light at or below 30°C (86°F) for up to 14 days.

If removed from the original carton, unopened vials of QALSODY can be removed from and returned to the refrigerator, if necessary, for not more than 6 hours per day at or below 30°C (86°F) for a maximum of 6 days (36 hours).

17 PATIENT COUNSELING INFORMATION

Myelitis and/or Radiculitis

Inform patients and caregivers that QALSODY could cause myelitis and radiculitis. Instruct patients and caregivers to contact their healthcare provider if symptoms consistent with these adverse reactions develop [see Warnings and Precautions (5.1)].

Papilledema and Elevated Intracranial Pressure

Inform patients and caregivers that QALSODY could cause papilledema and elevated intracranial pressure. Instruct patients and caregivers to contact their healthcare provider if symptoms consistent with these adverse reactions develop [see Warnings and Precautions (5.2)].

Aseptic Meningitis

Inform patients and caregivers that QALSODY could cause aseptic meningitis. Instruct patients and caregivers to contact their healthcare provider if symptoms consistent with meningitis develop [see Warnings and Precautions (5.3)].

57294-01

Manufactured by:
Biogen MA Inc.
Cambridge, MA 02142

QALSODY is a trademark of Biogen MA Inc.
© Biogen Inc.

Principal Display Panel - Carton Label

1 vial

NDC: 64406-109-01

QALSODY™
(tofersen) Injection

100 mg/15 mL
(6.7 mg/mL)

Sterile solution for
Intrathecal Injection Only

Rx only

Biogen®

Principal Display Panel - Vial Label

QALSODY™
(tofersen) Injection

100 mg/15 mL
(6.7 mg/mL)

Sterile solution for Intrathecal Injection Only

Rx only